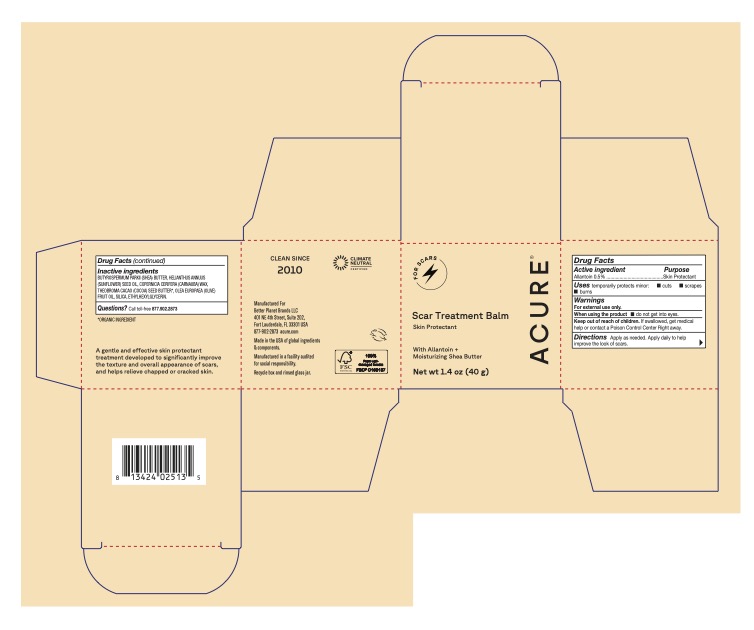 DRUG LABEL: Scar Treatment Balm
NDC: 54136-365 | Form: SALVE
Manufacturer: Better Planet Brands LLC
Category: otc | Type: HUMAN OTC DRUG LABEL
Date: 20251203

ACTIVE INGREDIENTS: ALLANTOIN, (R)- 0.5 g/100 g
INACTIVE INGREDIENTS: BUTYROSPERMUM PARKII (SHEA) BUTTER; COPERNICIA CERIFERA (CARNAUBA) WAX; SILICA; HELIANTHUS ANNUUS (SUNFLOWER) SEED OIL; ETHYLHEXYLGLYCERIN; OLEA EUROPAEA (OLIVE) FRUIT OIL; THEOBROMA CACAO (COCOA) SEED BUTTER

Scar Treatment Balm

Active Ingredients

Allantoin 0.5%

Purpose

Skin Protectant

Uses

temporarily protects minor:  cuts  scrapes

 burns

Warnings

For external use only

When using this product

• do not get into eyes.

Keep out of reach of children

If swallowed, get medical help or contact a Poison Control Center Right away.

Directions

Apply as needed. Apply daily to help improve the look of scars.

Inactive ingredients

BUTYROSPERMUM PARKII (SHEA) BUTTER, HELIANTHUS ANNUUS (SUNFLOWER) SEED OIL, COPERNICIA CERIFERA (CARNAUBA) WAX, THEOBROMA CACAO (COCOA) SEED BUTTER*, OLEA EUROPAEA (OLIVE) FRUIT OIL, SILICA,

Questions?

Call toll-free 877.902.2873